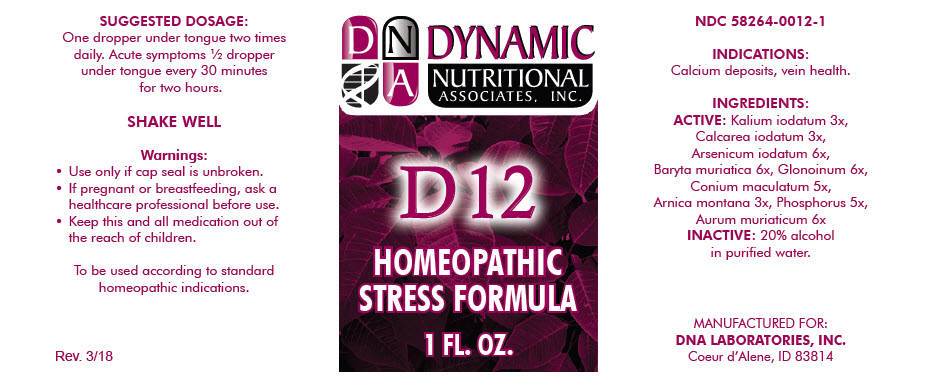 DRUG LABEL: D-12
NDC: 58264-0012 | Form: SOLUTION
Manufacturer: DNA Labs, Inc.
Category: homeopathic | Type: HUMAN OTC DRUG LABEL
Date: 20250113

ACTIVE INGREDIENTS: POTASSIUM IODIDE 3 [hp_X]/1 mL; CALCIUM IODIDE 3 [hp_X]/1 mL; ARSENIC TRIIODIDE 6 [hp_X]/1 mL; BARIUM CHLORIDE DIHYDRATE 6 [hp_X]/1 mL; NITROGLYCERIN 5 [hp_X]/1 mL; CONIUM MACULATUM FLOWERING TOP 5 [hp_X]/1 mL; ARNICA MONTANA 3 [hp_X]/1 mL; PHOSPHORUS 5 [hp_X]/1 mL; GOLD TRICHLORIDE 6 [hp_X]/1 mL
INACTIVE INGREDIENTS: ALCOHOL; WATER

D-12

NDC 58264-0012-1

INDICATIONS

PURPOSE

Calcium deposits, vein health.

INGREDIENTS

ACTIVE

Kalium iodatum 3x, Calcarea iodatum 3x, Arsenicum iodatum 6x, Baryta muriatica 6x, Glonoinum 6x, Conium maculatum 5x, Arnica montana 3x, Phosphorus 5x, Aurum muriaticum 6x

INACTIVE

20% alcohol in purified water.

SUGGESTED DOSAGE

One dropper under tongue two times daily. Acute symptoms ½ dropper under tongue every 30 minutes for two hours.

SHAKE WELL

Warnings

- Use only if cap seal is unbroken.

PREGNANCY OR BREAST FEEDING

- If pregnant or breastfeeding, ask a healthcare professional before use.

KEEP OUT OF REACH OF CHILDREN

- Keep this and all medication out of the reach of children.

To be used according to standard homeopathic indications.

PRINCIPAL DISPLAY PANEL - 1 FL. OZ. Bottle Label

DYNAMIC
NUTRITIONAL
ASSOCIATES, INC.

D 12

HOMEOPATHIC
STRESS FORMULA

1 FL. OZ.